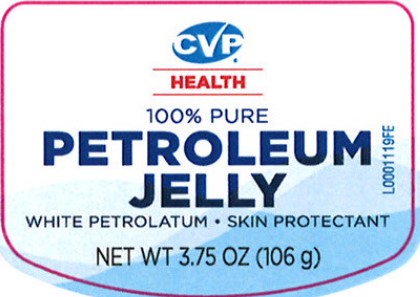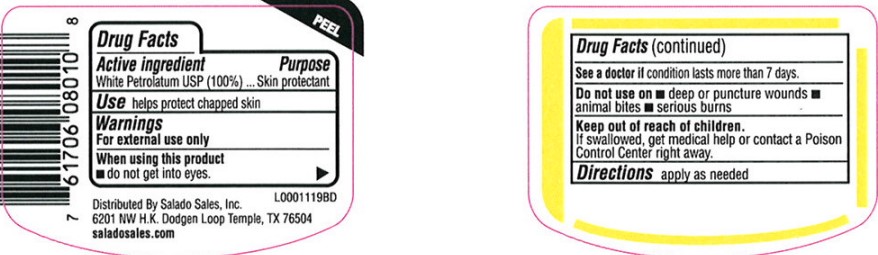 DRUG LABEL: Petroleum
NDC: 57243-069 | Form: JELLY
Manufacturer: Salado Sales Inc.
Category: otc | Type: HUMAN OTC DRUG LABEL
Date: 20260206

ACTIVE INGREDIENTS: PETROLATUM 1 g/1 g

CVP 069.001/069AA
Petroleum Jelly

Active ingredients

White Petrolatum USP (100%)

Purpose

Skin Protectant

Use

helps protect chapped skin

Warnings

For external use only

When using this product

- do not get into eyes

See a doctor if

condition lasts more than 7 days

Do not use on

- deep or puncture wounds
- animal bites
- serious burns

Keep out of reach of children

If swallowed, get medical help or contact a Poison Control Center right away.

Directions

apply as needed

Inactive Ingredient

None

Adverse Reactions

Distributed by Salado Sales, Inc.

6201 NW H.K. Dodgen Loop Temple, TX 76504

saladosales.com

Principal display panel

CVP

100% PURE

PETROLEUM JELLY

WHITE PETROLATUM

SKIN PROTECTANT

NET WT 3.75 OZ (106 g)